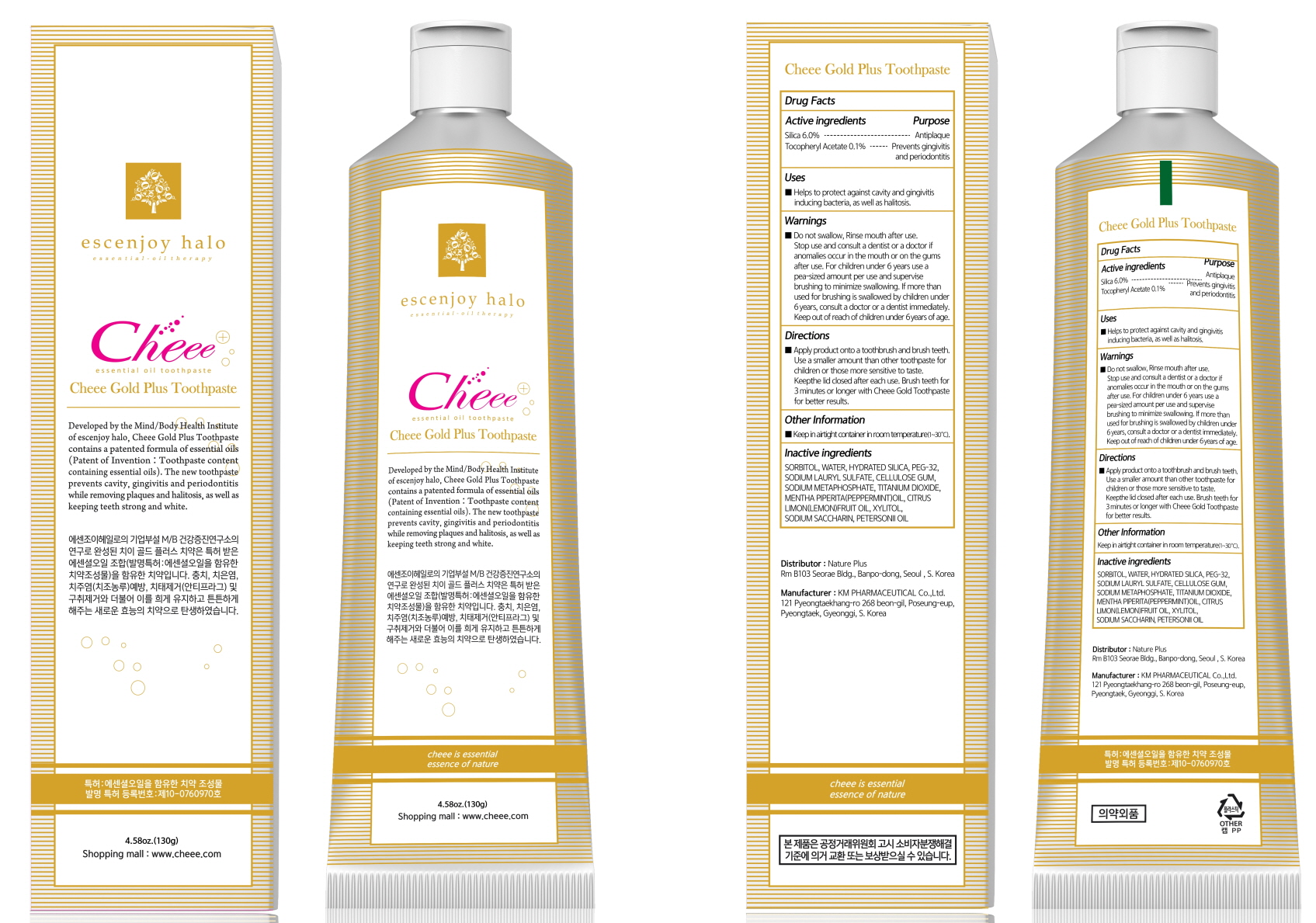 DRUG LABEL: Cheee Gold Plus Tooth
NDC: 79428-010 | Form: PASTE, DENTIFRICE
Manufacturer: Nature Plus
Category: otc | Type: HUMAN OTC DRUG LABEL
Date: 20200707

ACTIVE INGREDIENTS: SILICON DIOXIDE 7.8 g/130 g; .ALPHA.-TOCOPHEROL ACETATE 0.13 g/130 g
INACTIVE INGREDIENTS: SORBITOL; WATER; HYDRATED SILICA

ACTIVE INGREDIENTS

Silica 6.0%
Tocopheryl Acetate 0.1%

INACTIVE INGREDIENTS

SORBITOL, WATER, HYDRATED SILICA, PEG-32, SODIUM LAURYL SULFATE, CELLULOSE GUM, SODIUM METAPHOSPHATE, TITANIUM DIOXIDE, MENTHA PIPERITA(PEPPERMINT)OIL, CITRUS LIMON(LEMON)FRUIT OIL, XYLITOL, SODIUM SACCHARIN, PETERSONII OIL

PURPOSE

Antiplaque
Prevents gingivitis and periodontitis

WARNINGS

Do not swallow, Rinse mouth after use. Stop use and consult a dentist or a doctor if anomalies occur in the mouth or on the gums after use. For children under 6 years use a pea-sized amount per use and supervise brushing to minimize swallowing. If more than used for brushing is swallowed by children under 6 years, consult a doctor or a dentist immediately. Keep out of reach of children under 6 years of age.

Keep out of reach of children under 6 years of age.

Uses

Helps to protect against cavity and gingivitis inducing bacteria, as well as halitosis.

Directions

Apply product onto a toothbrush and brush teeth. Use a smaller amount than other toothpaste for children or those more sensitive to taste. Keep the lid closed after each use. Brush teeth for 3 minutes or longer with Cheee Gold Toothpaste for better results.

Other Information

Keep in airtight container in room temperature(1~30°C).